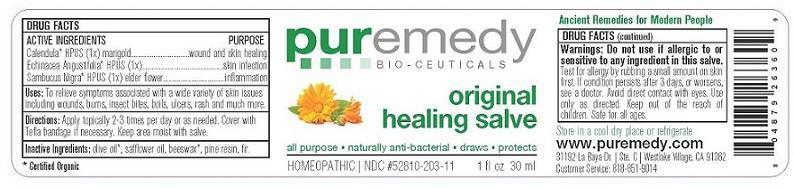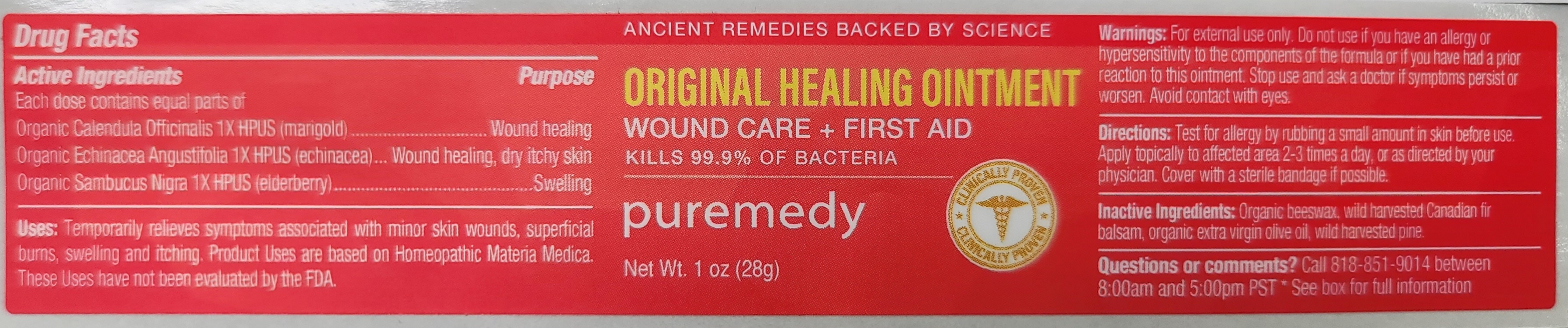 DRUG LABEL: ORIGINAL HEALING
NDC: 52810-213 | Form: SALVE
Manufacturer: PUREMEDY
Category: homeopathic | Type: HUMAN OTC DRUG LABEL
Date: 20240111

ACTIVE INGREDIENTS: SAMBUCUS NIGRA FLOWER 1 [hp_X]/100 mL; CALENDULA OFFICINALIS FLOWER 1 [hp_X]/100 mL; ECHINACEA ANGUSTIFOLIA 1 [hp_X]/100 mL
INACTIVE INGREDIENTS: YELLOW WAX; OLIVE OIL; CANADA BALSAM; PINE NEEDLE OIL (PINUS SYLVESTRIS)

ORIGINAL HEALING (52810-213)

ACTIVE INGREDIENTS

ORG. SAMBUCUS NIGRA (1X) HPUS (ELDER BARK AND FLOWER)

ORG. CALENDULA OFFICINALIS (1X) HPUS) (MARIGOLD)

ORG. ECHINACEA ANGUST. (1X) HPUS (ECHINACEA)

PURPOSE

PROPERTIES

SKIN PROTECTANT

ANTI-INFLAMMATORY

PROMOTES SKIN HEALING

REMEDY FOR WOUNDS

INDICATIONS AND USAGE

USES: TO RELIEVE SYMPTOMS ASSOCIATED WITH SKIN IRRITATIONS, WOUNDS, BOILS, CUTS, ITCH, BURNS, TOPICAL INFECTION, AND A WIDE VARIETY OF SKIN AILMENTS.

DOSAGE AND ADMINISTRATION

DIRECTIONS: APPLY TO AFFECTED AREA 2-4 TIMES PER DAY OR AS NEEDED. COVER WITH A BANDAID OR TELFA BANDAGE IF NECESSARY. DO NOT DRESS WITH GAUZE.

INACTIVE INGREDIENT

OTHER INGREDIENTS: ORG. EXTRA VIRGIN OLIVE OIL, ORG. BEESWAX, FIR BALSAM RESIN

WARNINGS

WARNING: TEST FOR ALLERGY BY RUBBING A SMALL AMOUNT ON SKIN FIRST. DO NOT USE IF ALLERGIC TO OR HYPER-SENSITIVE TO ANY INGREDIENT IN THIS SALVE. IF CONDITION PERSISTS OR WORSENS CONSULT YOUR HEALTH CARE PROVIDER. (* = CERTIFIED ORGANIC INGREDIENTS)

KEEP OUT OF REACH OF CHILDREN.

QUESTIONS

CUSTOMER SERVICE 310-526-6108